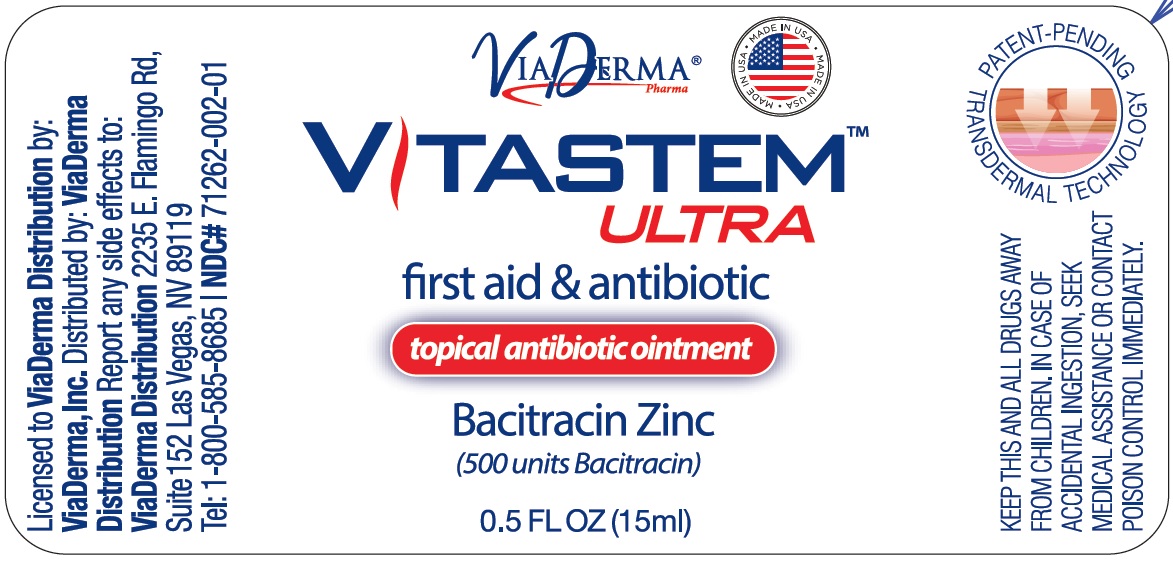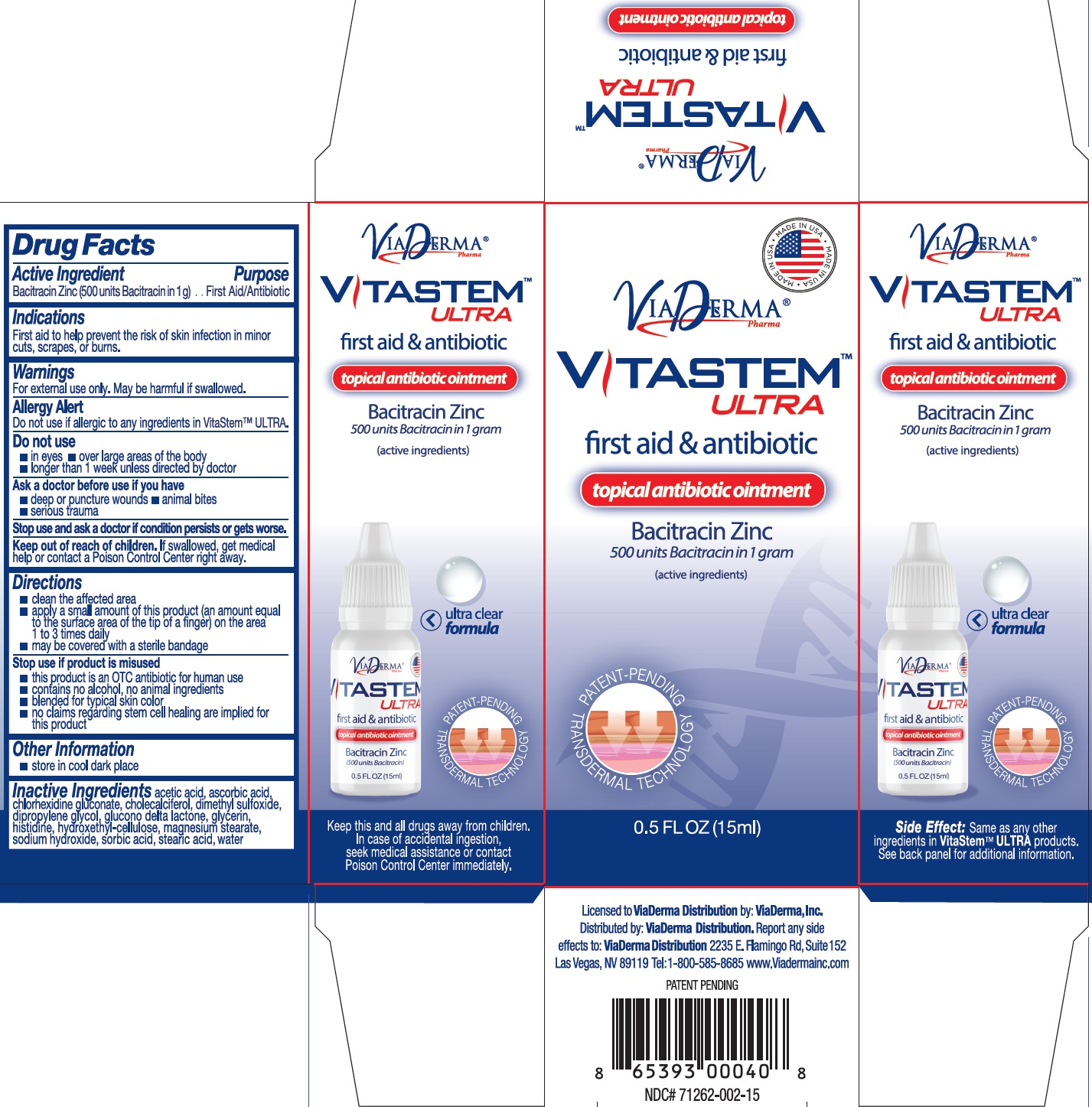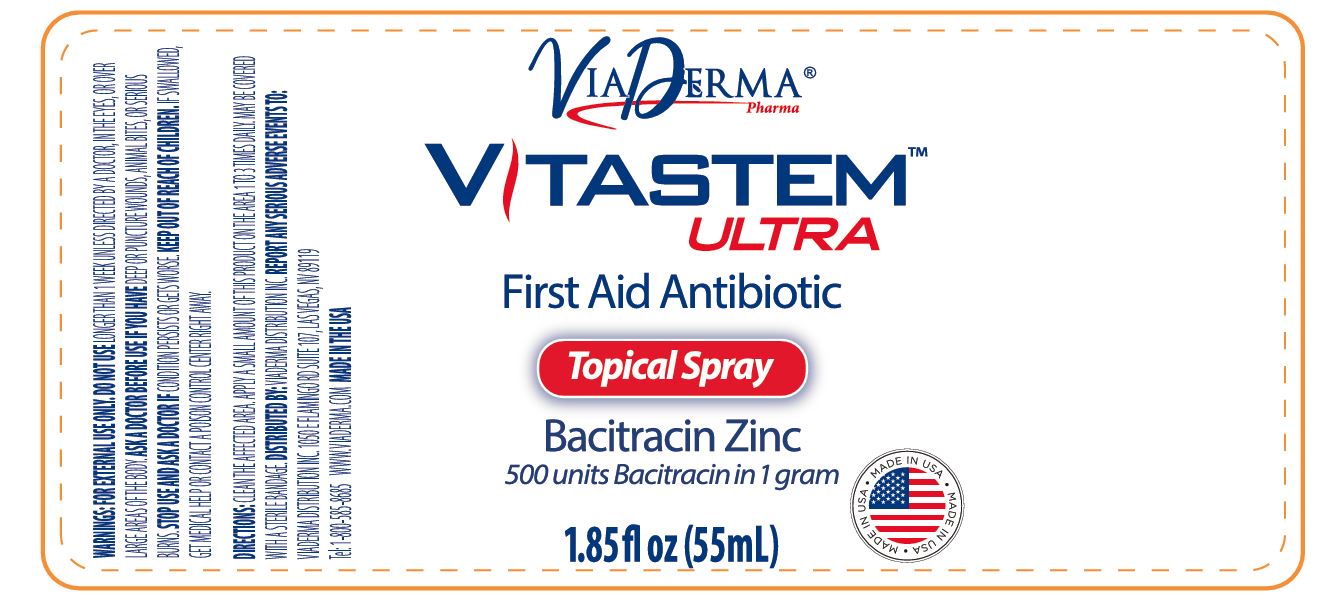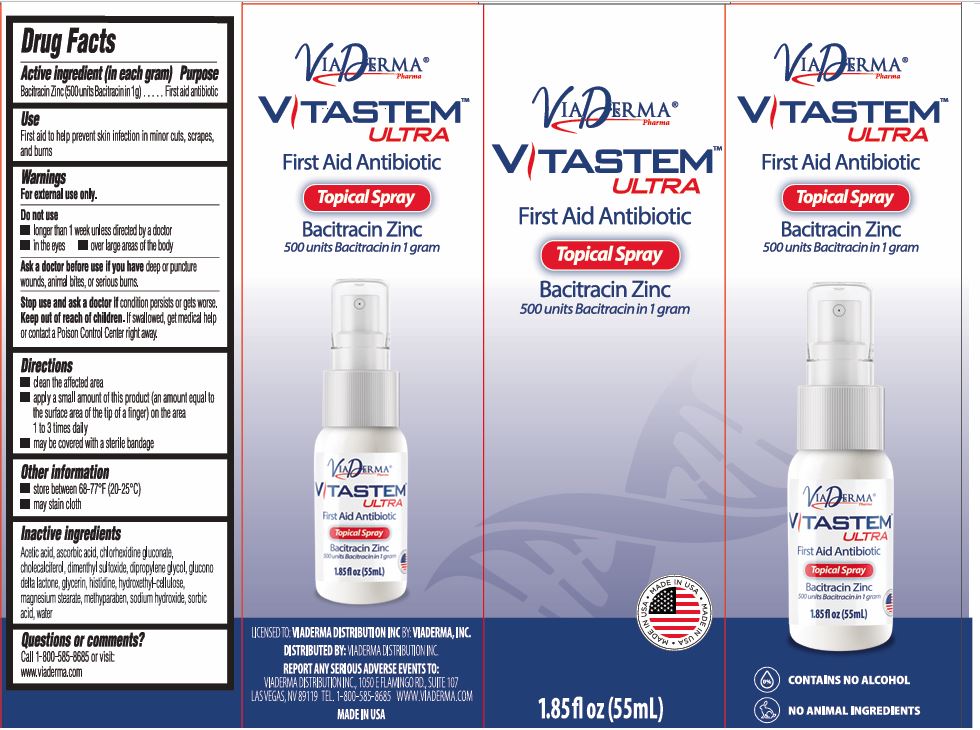 DRUG LABEL: Vitastem ULTRA
NDC: 71262-007 | Form: OINTMENT
Manufacturer: ViaDerma Distribution, Inc
Category: otc | Type: HUMAN OTC DRUG LABEL
Date: 20250403

ACTIVE INGREDIENTS: BACITRACIN ZINC 500 U/1 mL
INACTIVE INGREDIENTS: ACETIC ACID; ASCORBIC ACID; CHLORHEXIDINE GLUCONATE; CHOLECALCIFEROL; DIMETHYL SULFOXIDE; DIPROPYLENE GLYCOL; GLUCONOLACTONE; GLYCERIN; HISTIDINE; HYDROXYETHYL CELLULOSE, UNSPECIFIED; MAGNESIUM STEARATE; SODIUM HYDROXIDE; SORBIC ACID; STEARIC ACID; WATER

Vitastem ULTRA

Active Ingredient

Bacitracin Zinc (500 units Bacitracin in 1g)

Purpose

First Aid/Antibiotic

Uses

First aid to help prevent the risk of skin infection in minor cuts, scrapes, or burns.

Warnings

For external use only. May be harmful if swallowed.

Allergy Alert

Do not use if allergic to any ingredients in VitaStem™ ULTRA.

Do not use

- in eyes
- over large areas of the body
- longer than 1 week unless directed by doctor

Ask a doctor before use if you have

- deep or punture wounds
- animal bites
- serious trauma

Stop use and ask a doctor if

condition persists or gets worse.

Keep out of reach of children.

If swallowed, get medical help or contact a Poison Control Center right away.

Directions

- clean the affected area
- apply a small amount of this product (an amount equal to the surface area of the tip of a finger) on the area 1 to 3 times daily
- may be covered with a sterile bandage

- this product is an OTC antibiotic for human use
- contains no alcohol, no animal ingredients
- blended for typical skin color
- no claims regarding stem cell healing are implied for this product

Stop use if product is misused

Other Information

- store in a cool dry place

Inactive Ingredients

acetic acid, ascorbic acid, chlorhexidine gluconate, cholecalciferol, dimethyl sulfoxide, dipropylene glycol, glucono delta lactone, glycerin, histidine, hydroxethyl cellulose, magnesium stearate, sodium hydroxide, sorbic acid, stearic acid, water